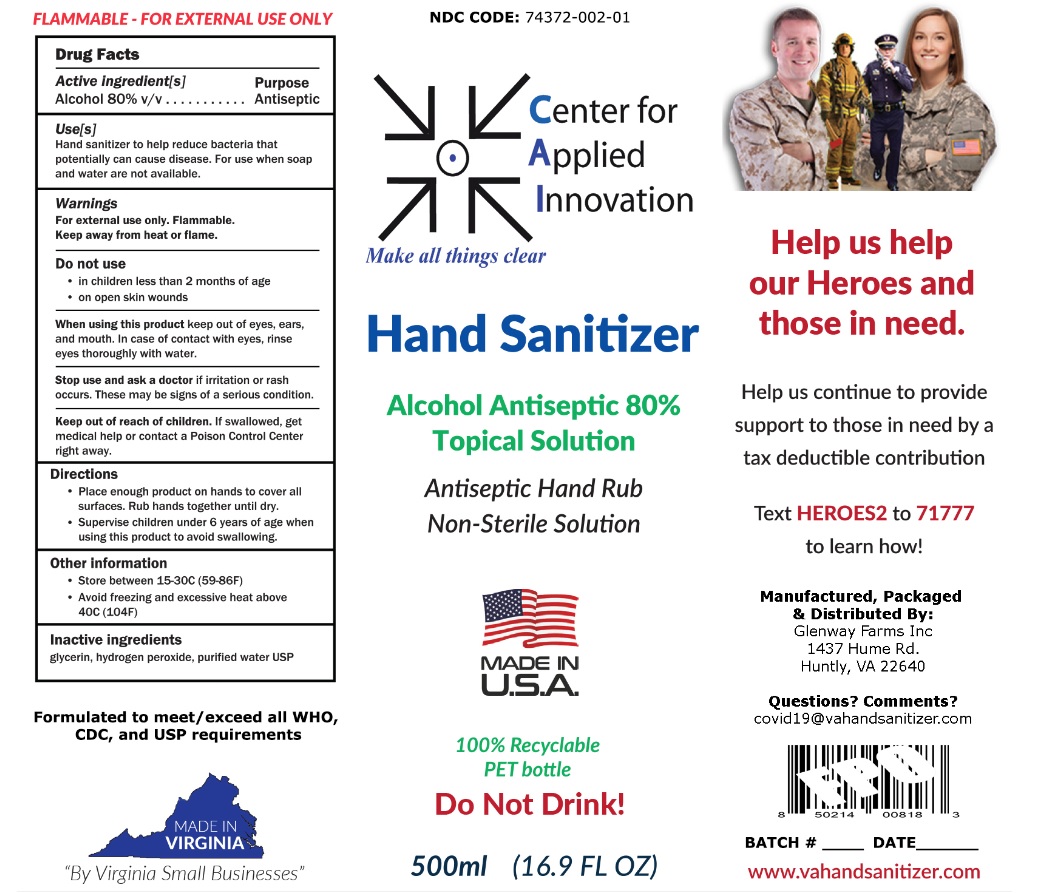 DRUG LABEL: Center for Applied Innovation LLC Hand Sanitizer
NDC: 74372-002 | Form: SOLUTION
Manufacturer: GLENWAY FARMS, INC.
Category: otc | Type: HUMAN OTC DRUG LABEL
Date: 20200820

ACTIVE INGREDIENTS: ALCOHOL 80 mL/100 mL
INACTIVE INGREDIENTS: GLYCERIN; HYDROGEN PEROXIDE; WATER

Center for Applied Innovation LLC Hand Sanitizer

Active ingredient[s]

Alcohol 80% v/v

Purpose

Antiseptic

Uses[s]

Hand sanitizer to help reduce bacteria that potentially can cause disease. For use when soap and water are not available.

Warnings

For external use only. Flammable.

Keep away from heat or flame.

Do not use

- in children less than 2 months of age
- on open skin wounds

When using this product keep out of eyes, ears, and mouth. In case of contact with eyes, rinse eyes thoroughly with water.

Stop use and ask a doctor if irritation or rash occurs. These may be signs of a serious condition.

Keep out of reach of children. If swallowed, get medical help or contact a Poison Control Center right away.

Directions

- Place enough product on hands to cover all surfaces. Rub hands together until dry.
- Supervise children under 6 years of age when using this product to avoid swallowing.

Other information

- Store between 15-30C (59-86F)
- Avoid freezing and excessive heat above 40C (104F)

Inactive Ingredients

glycerin, hydrogen peroxide, purified water USP

Make all things clear

Alcohol Antiseptic 80%

Topical Solution

Antiseptic Hand Rub

Non-Sterile Solution

MADE IN U.S.A

100% Recyclable PET bottle

Do Not Drink!

Help us help our Heroes and those in need.

Help us continue to provide support to those in need by a tax deductible contribution

Text HEROES2 to 71777 to learn how!

Manufactured, Packaged and Distributed By:

Glenway Farms Inc

1437 Hume Rd.

Huntly, VA 22640

Questions? Comments?

covid19@vahandsanitizer.com

www.vahandsanitizer.com

FLAMMABLE FOR EXTERNAL USE ONLY

Formulated to meet/exceed all WHO, CDC, and USP requirements

MADE IN VIRGINIA

"By Virginia Small Businesses"